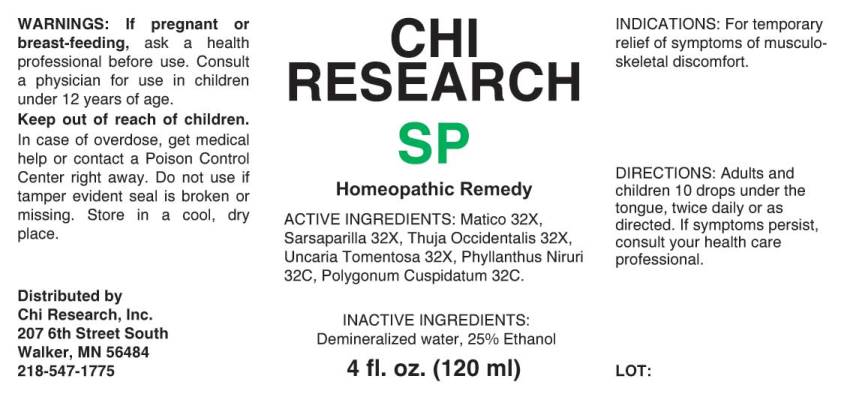 DRUG LABEL: SP
NDC: 52654-0006 | Form: LIQUID
Manufacturer: Chi Research, Inc.
Category: homeopathic | Type: HUMAN OTC DRUG LABEL
Date: 20240422

ACTIVE INGREDIENTS: PIPER ADUNCUM LEAF 32 [hp_X]/1 mL; SMILAX ORNATA WHOLE 32 [hp_X]/1 mL; THUJA OCCIDENTALIS LEAFY TWIG 32 [hp_X]/1 mL; UNCARIA TOMENTOSA ROOT 32 [hp_X]/1 mL; PHYLLANTHUS NIRURI WHOLE 32 [hp_C]/1 mL; REYNOUTRIA JAPONICA WHOLE 32 [hp_C]/1 mL
INACTIVE INGREDIENTS: WATER; ALCOHOL

DRUG FACTS:

ACTIVE INGREDIENTS:

Matico 32X, Sarsaparilla (Smilax Regelii) 32X, Thuja Occidentalis 32X, Uncaria Tomentosa 32X, Phyllanthus Niruri 32C, Polygonum Cuspidatum 32C.

INDICATIONS:

For temporary relief of symptoms of musculoskeletal discomfort.

WARNINGS:

If pregnant or breast-feeding, ask a health professional before use. Consult a physician for use in children under 12 years of age.

Keep out of reach of children. In case of overdose, get medical help or contact a Poison Control Center right away.

Do not use if tamper evident seal is broken or missing. Store in a cool, dry place.

KEEP OUT OF REACH OF CHILDREN:

In case of overdose, get medical help or contact a Poison Control Center right away.

DIRECTIONS:

Adults and children 10 drops under the tongue, twice daily or as directed. If symptoms persist, consult your health care professional.

INDICATIONS:

For temporary relief of symptoms of musculoskeletal discomfort.

INACTIVE INGREDIENTS:

Demineralized water, 25% Ethanol

QUESTIONS:

Distributed by

Chi Research, Inc.

207 6th Street South

Walker, MN 56484

218-547-1775

PACKAGE LABEL DISPLAY:

CHI

RESEARCH

SP

Homeopathic Remedy

4 fl. oz. (120 ml)